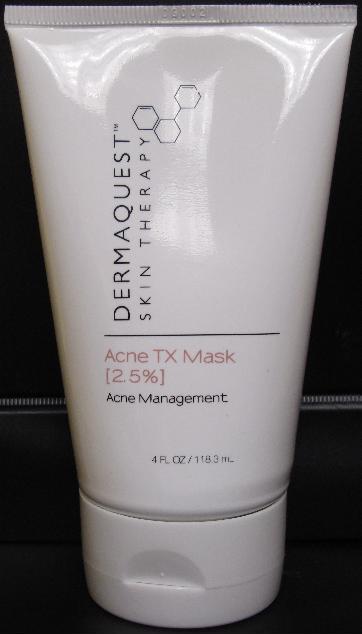 DRUG LABEL: Acne TX Mask
NDC: 62742-4050 | Form: CREAM
Manufacturer: Allure Labs, Inc.
Category: otc | Type: HUMAN OTC DRUG LABEL
Date: 20100810

ACTIVE INGREDIENTS: BENZOYL PEROXIDE 25 mg/1 mL

Drug Facts

INDICATIONS AND USAGE:

Formulated as a home treatment for acne-prone skin, this mask gently exfoliates the skin's surface with jojoba beads, allowing the follicular-oxidizing benefits of Benzoyl Peroxide to penetrate and take effect. Plant extracts and MSM are also included to increase healing time and assist in preventing future breakouts.

DIRECTIONS:
Apply to cleansed skin using fingertips. Massage gently in circular movements for 1-2 minutes and then allow the product to remain on the skin for an additional 5-10 minutes, depending on skin tolerance and/or sensitivity. Avoid the eye area. Rinse well and follow suggested post-mark home care reigimen. Use this product according the recommendations of your skin care professional. Skip the massage step with Grade 3 and 4 Acne.

ACTIVE INGREDIENT:

Benzoyl Peroxide 2.5%

INACTIVE INGREDIENTS:

Water (Aqua), Butylene Glycol, Jojoba Esters, Glycerin, Sorbitol, Dimethyl Sulfone, Silver, Polysorbate-20, Caprylyl Glycol, Salix alba (Willow) Bark Extract, Carbomer, Triethanolamine, Phenoxyethanol, Extracts of Malva Sylvestris (Mallow), Mentha piperita (Peppermint) Leaf, Primula Veris, Alchemilla vulgaris, Veronica Officinalis, Melissa Officinalis Leaf, Achillea Millefolium, Melia Azadiracta (Neem) Leaf Extract, PEG-60 Almond Glycerides-Nordihydroguaiaretic Acid-Oleanolic Acid, Sodium Benzoate, Disodium EDTA

PACKAGE LABEL

DISTRIBUTOR:

Dermaquest, Inc

Hayward, CA

www.dermaquestinc.com

PRINCIPAL DISPLAY PANEL: